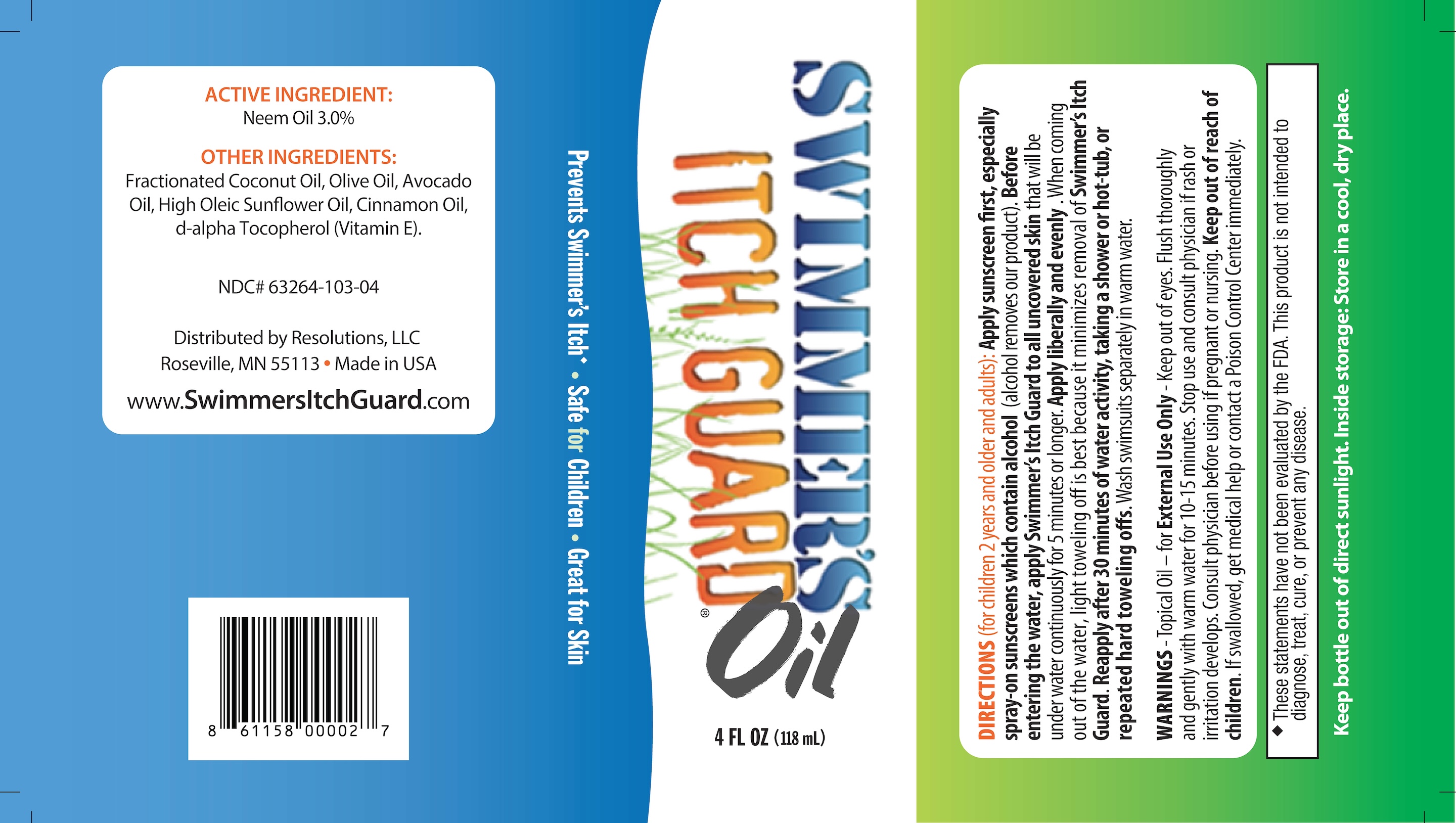 DRUG LABEL: Swimmers Itch Guard
NDC: 63264-103 | Form: OIL
Manufacturer: Resolutions, LLC
Category: homeopathic | Type: HUMAN OTC DRUG LABEL
Date: 20250421

ACTIVE INGREDIENTS: AZADIRACHTA INDICA SEED OIL 0.03 g/100 g
INACTIVE INGREDIENTS: SUNFLOWER OIL; CINNAMON OIL; MEDIUM-CHAIN TRIGLYCERIDES; .ALPHA.-TOCOPHEROL, D-; OLIVE OIL; AVOCADO OIL

Swimmer's Itch Guard Oil

Active ingredients

Neem Oil 3%

Warnings

Topical Oil – for External Use Only

Keep out of eyes. Flush thoroughly and gently with warm water for 10-15 minutes.

Stop use and consult physician if rash or irritation develops.

ASK DOCTOR

Consult physician before using if pregnant or nursing.

Keep out of reach of children. If swallowed, get medical help or contact a Poison Control Center immediately.

Directions

(for children 2 years and older and adults): Apply sunscreen first, especially spray-on sunscreens which contain alcohol (alcohol removes our product). Before entering the water, apply Swimmer’s Itch Guard to all uncovered skin that will be under water continuously for 5 minutes or longer. Apply liberally and evenly. When coming out of the water, light toweling off is best because it minimizes removal of Swimmer’s Itch Guard. Reapply after 30 minutes of water activity, taking a shower or hot-tub, or repeated hard toweling offs. Wash swimsuits separately in warm water.

OTHER SAFETY INFORMATION

These statements have not been evaluated by the FDA. This product is not intended to diagnose, treat, cure, or prevent any disease.

Inactive ingredients

Fractionated Coconut Oil, Olive Oil, Avocado Oil, High Oleic Sunflower Oil, Cinnamon Oil, d-alpha Tocopherol (Vitamin E)

INDICATIONS AND USAGE

Swimmers itch oil

PURPOSE

Swimmers itch oil